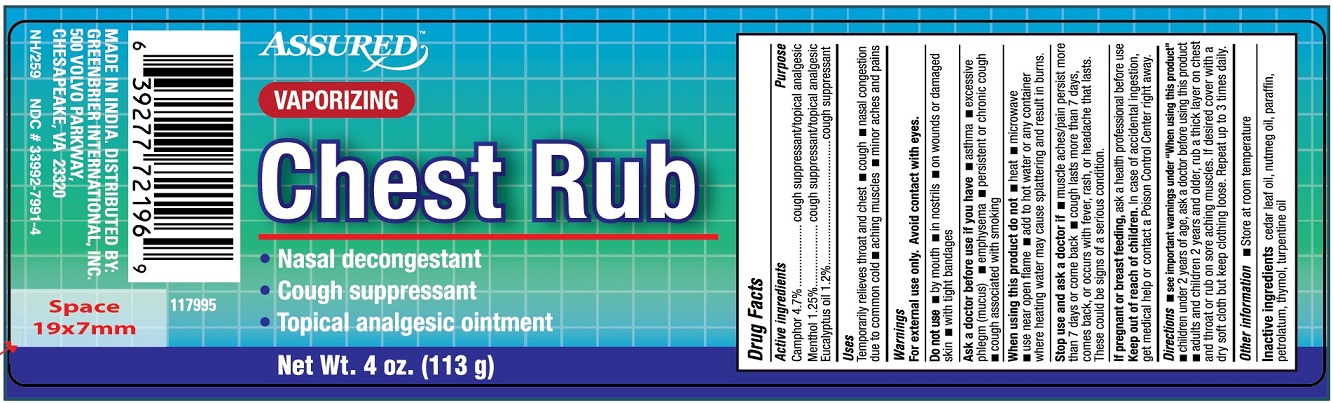 DRUG LABEL: Assured Vaporizing Chest Rub
NDC: 33992-7991 | Form: OINTMENT
Manufacturer: Greenbrier International, Inc.
Category: otc | Type: HUMAN OTC DRUG LABEL
Date: 20190119

ACTIVE INGREDIENTS: CAMPHOR (SYNTHETIC) 4.7 g/100 g; EUCALYPTUS OIL 1.2 g/100 g; MENTHOL 1.25 g/100 g
INACTIVE INGREDIENTS: CEDAR LEAF OIL; NUTMEG OIL; MINERAL OIL; PETROLATUM; THYMOL; TURPENTINE OIL

Active ingredients

Camphor 4.7%

Menthol 1.25%

Eucalyptus Oil 1.2%

Purpose

Cough suppressant/topical analgesic

Cough suppressant/topical analgesic

Cough suppressant

Uses

Temporarily relieves throat and chest

- cough
- nasal congestion due to common cold
- aching muscles
- minor aches and pains

Warnings

For external use only. Avoid contact with eyes.

Do not use

- by mouth
- in nostrils
- on wounds or damaged skin
- with tight bandages

Ask a doctor before use if you have

- asthama
- excessive phlegm (mucus)
- emphysema
- persistent or chronic cough
- cough associated with smoking

When using this product do not

- heat
- microwave
- use near open flame
- add to hot water or any container where heating water may cause splattering and result in burns

Stop use and ask a doctor if

- muscle aches/pain persist more than 7 days or come back
- cough lasts more than 7 days, comes back, or occurs with fever, rash or headache that lasts. These could be signs of a serious conditions.

PREGNANCY OR BREAST FEEDING

If pregnant or breast feeding, ask a health professional before use.

Keep out of reach of children. In case of accidental ingestion, get medical help or contact a Poison Control Centre right away.

Directions

- see important warnings under "When using this product"
- children under 2 years of age, ask a doctor before using this product
- adults and children 2 years and older, rub a thick layer on chest and throat or rub on sore aching muscles. If desired, cover with a dry soft cloth but keep clothing loose. Repeat up to 3 times daily.

Other information

- Store at room temperature

Inactive ingredients

cedar leaf oil, nutmeg oil, paraffin, petrolatum, thymol, turpentine oil

PACKAGE LABEL

PRINCIPAL DISPLAY PANEL

ASSURED VAPORIZING CHEST RUB